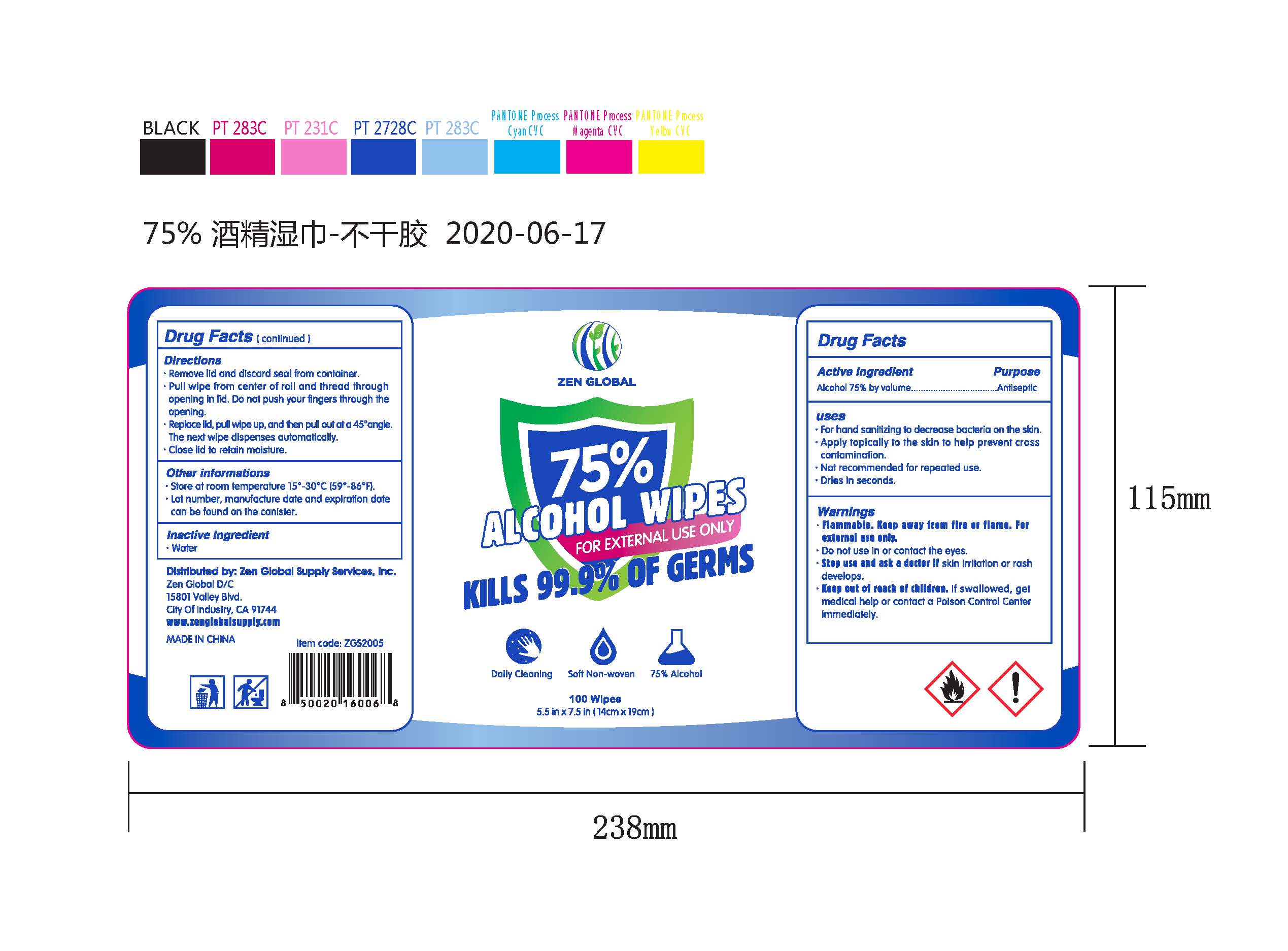 DRUG LABEL: Zen Global Alcohol Wipes
NDC: 75109-514 | Form: CLOTH
Manufacturer: Kangna (Zhejiang) Medical Supplies Co., Ltd.
Category: otc | Type: HUMAN OTC DRUG LABEL
Date: 20220114

ACTIVE INGREDIENTS: ALCOHOL 75 mL/100 mL
INACTIVE INGREDIENTS: WATER

75109-514 75% alcohol Zen Global Alcohol Wipes

Active Ingredient

Ethanol 75% by volume

Purpose

Antiseptic

USE

for hand sanitizing to decrease bacteria on the skin

apply topically to the skin to help prevent cross contamination

not recommended for repeated use

dries in seconds

Warning

●Flammable. Keep away from fire or flame. For
external use only.
●Do not use in or contact the eyes.
●Stop use and ask a doctor if skin irritation or rash
develops.

Keep out of reach of children

If swallowed, get medical help or call Poison Control Center immediately.

Directions

Remove lid and discard seal from container.
Pull wipe from center of roll and thread through
opening in lid. Do not push your fingers through the
opening.
●Replace lid, pull wipe up, and then pull out at a 45°angle.
The next wipe dispenses automatically.
. Close lid to retain moisture.
Other informations
Store at room temperature 15°- 30°C (59°-86°F).
●Lot number, manufacture date and expiration date
can be found on the canister.

Inactive ingredients

Water